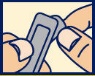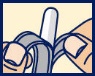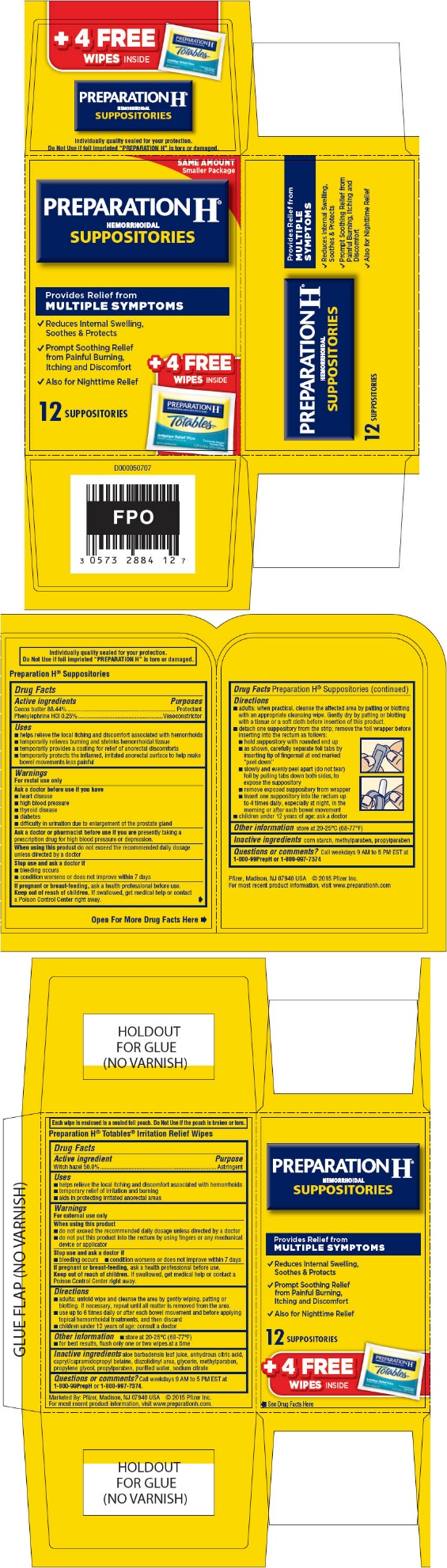 DRUG LABEL: Preparation H
NDC: 0573-2884 | Form: KIT | Route: RECTAL
Manufacturer: Haleon US Holdings LLC
Category: otc | Type: HUMAN OTC DRUG LABEL
Date: 20240405

ACTIVE INGREDIENTS: COCOA BUTTER 2211 mg/1 1; PHENYLEPHRINE HYDROCHLORIDE 6.25 mg/1 1; WITCH HAZEL 5 g/1 1
INACTIVE INGREDIENTS: STARCH, CORN; METHYLPARABEN; PROPYLPARABEN; ALOE VERA LEAF; ANHYDROUS CITRIC ACID; CAPRYL/CAPRAMIDOPROPYL BETAINE; DIAZOLIDINYL UREA; GLYCERIN; METHYLPARABEN; PROPYLENE GLYCOL, (R)-; PROPYLPARABEN; WATER; SODIUM CITRATE, UNSPECIFIED FORM

Drug Facts

Active Ingredients

Cocoa butter 88.44%

Phenylephrine HCl 0.25%

Purposes

Protectant

Vasoconstrictor

Uses

- helps relieve the local itching and discomfort associated with hemorrhoids
- temporarily relieves burning and shrinks hemorrhoidal tissue
- temporarily provides a coating for relief of anorectal discomforts
- temporarily protects the inflamed, irritated anorectal surface to help make bowel movements less painful

Warnings

For rectal use only

Ask a doctor before use if you have

- heart disease
- high blood pressure
- thyroid disease
- diabetes
- difficulty in urination due to enlargement of the prostate gland

Ask a doctor or pharmacist before use if you arepresently taking a prescription drug for high blood pressure or depression.

WHEN USING

When using this productdo not exceed the recommended daily dosage unless directed by a doctor

Stop use and ask a doctor if

- bleeding occurs
- condition worsens or does not improve within 7 days

PREGNANCY OR BREAST FEEDING

If pregnant or breast-feeding,ask a health professional before use.

Keep out of reach of children.If swallowed, get medical help or contact a Poison Control Center right away.

Directions

- adults: when practical, cleanse the affected area by patting or blotting with an appropriate cleansing wipe. Gently dry by patting or blotting with a tissue or a soft cloth before insertion of this product.
- detach one suppository from the strip; remove the foil wrapper before inserting into the rectum as follows:

1. hold suppository with rounded end up
2. as shown, carefully separate foil tabs by inserting tip of fingernail at end marked "peel down"
3. slowly and evenly peel apart (do not tear) foil by pulling tabs down both sides, to expose the suppository
4. remove exposed suppository from wrapper
5. insert one suppository into the rectum up to 4 times daily, especially at night, in the morning or after each bowel movement

- children under 12 years of age: ask a doctor

Other information

store at 20-25°C (68-77°F)

Inactive ingredients

corn starch, methylparaben, propylparaben

Questions or comments?

Call weekdays 9 AM to 5 PM EST at 1-800-99PrepH or 1-800-997-7374

For most recent product information, visit www.preparationh.com

Preparation H®Totables®Irritation Relief Wipes

Drug Facts

Active ingredient

Witch hazel 50.0%

Purpose

Astringent

Uses

- helps relieve the local itching and discomfort associated with hemorrhoids
- temporary relief of irritation and burning
- aids in protecting irritated anorectal areas

Warnings

For external use only

When using this product

- do not exceed the recommended daily dosage unless directed by a doctor
- do not put this product into the rectum by using fingers or any mechanical device or applicator

Stop use and ask a doctor if

- bleeding occurs
- condition worsens or does not improve within 7 days

PREGNANCY OR BREAST FEEDING

If pregnant or breast-feeding,ask a health professional before use.

Keep out of reach of children.If swallowed, get medical help or contact a Poison Control Center right away.

Directions

- adults: unfold wipe and cleanse the area by gently wiping, patting or blotting. If necessary, repeat until all matter is removed from the area.
- use up to 6 times daily or after each bowel movement and before applying topical hemorrhoidal treatments, and then discard
- children under 12 years of age: consult a doctor

Other information

- store at 20-25°C (68-77°F)
- for best results, flush only one or two wipes at a time

Inactive ingredients

aloe barbadensis leaf juice, anhydrous citric acid, capryl/capramidopropyl betaine, diazolidinyl urea, glycerin, methylparaben, propylene glycol, propylparaben, purified water, sodium citrate

Questions or comments?

Call weekdays 9 AM to 5 PM EST at 1-800-99PrepHor 1-800-997-7374.

For most recent product information, visit www.preparationh.com.

PRINCIPAL DISPLAY PANEL - Kit Carton

SAME AMOUNT
Smaller Package

PREPARATION H®
HEMORRHOIDAL
SUPPOSITORIES

Provides Relief from
MULTIPLE SYMPTOMS

- Reduces Internal Swelling,
  Soothes & Protects
- Prompt Soothing Relief
  from Painful Burning,
  Itching and Discomfort
- Also for Nighttime Relief

+ 4 FREE
WIPESINSIDE

12 SUPPOSITORIES